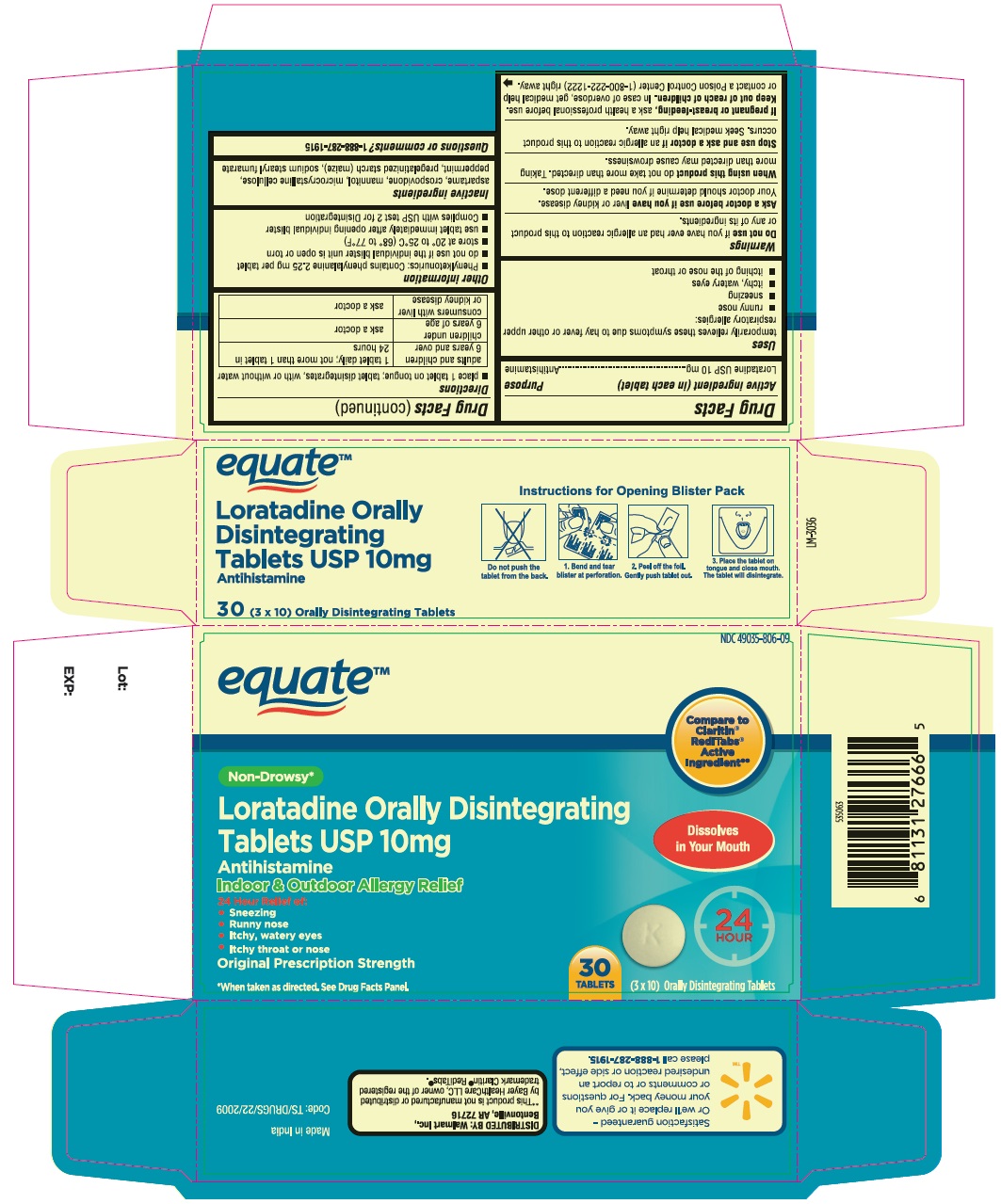 DRUG LABEL: Loratadine ODT
NDC: 49035-806 | Form: TABLET, ORALLY DISINTEGRATING
Manufacturer: Wal-Mart Stores, Inc.
Category: otc | Type: Human OTC Drug Label
Date: 20221104

ACTIVE INGREDIENTS: LORATADINE 10 mg/1 1
INACTIVE INGREDIENTS: ASPARTAME; CROSPOVIDONE (15 MPA.S AT 5%); MANNITOL; MICROCRYSTALLINE CELLULOSE; PEPPERMINT; STARCH, CORN; SODIUM STEARYL FUMARATE

Loratadine Orally Disintegrating Tablets USP 10 mg

Active ingredient (in each tablet)

Loratadine USP 10 mg

Purpose

Antihistamine

Uses

temporarily relieves these symptoms due to hay fever or other upper respiratory allergies:

- runny nose
- sneezing
- itchy, watery eyes
- itching of the nose or throat

Do not use

if you have ever had an allergic reaction to this product or any of its ingredients.

Ask a doctor before use if you have

liver or kidney disease. Your doctor should determine if you need a different dose.

When using this product

do not take more than directed. Taking more than directed may cause drowsiness.

Stop use and ask a doctor if

an allergic reaction to this product occurs. Seek medical help right away.

If pregnant or breast-feeding,

ask a health professional before use.

Keep out of reach of children.

In case of overdose, get medical help or contact a Poison Control Center (1-800-222-1222) right away.

Directions

- place 1 tablet on tongue; tablet disintegrates, with or without water

adults and children 6 years and over | 1 tablet daily; not more than 1 tablet in 24 hours
children under 6 years of age | ask a doctor
consumers with liver or kidney disease | ask a doctor

Other information

- Phenylketonurics: Contains phenylalanine 2.25 mg per tablet
- do not use if the individual blister unit is open or torn
- store at 20° to 25°C (68° to 77°F)
- use tablet immediately after opening individual blister
- Complies with USP test 2 for Disintegration

Inactive ingredients

aspartame, crospovidone, mannitol, microcrystalline cellulose, peppermint, pregelatinized starch (maize), sodium stearyl fumarate

Questions or comments?

DISTRIBUTED BY: Walmart Inc,.
Bentonville, AR 72716
This Product is not manufactured or distributed
by Bayer HealthCare LLC, distributor of claritin®RediTabs®
Manufactured for :
AUROHEALTH LLC
2572 Brunswick Pikg
Lawrenceville, NJ 08684
Manufactured by :
Aurobindo Pharma Limited
Unit- VII (SEZ)
Mahabubnagar (Dt) -509302
India

PACKAGE LABEL-PRINCIPAL DISPLAY PANEL - 10 mg, Blister Carton 30 (3 x 10) Orally Disintegrating Tablets

NDC 49035-806-09

equateTM

Compared to
the active

Ingredient

In Claritin®

RediTabs®**

Non-Drowsy*

Loratadine Orally Disintegrating Dissolves

Tablets USP 10 mg in Your Mouth
Antihistamine

Indoor & Outdoor Allergy Relief

24 Hour Relief Of:

- Sneezing
- Runny nose 24
- Itchy, watery eyes HOUR
- Itchy throat or nose

Original Prescription Strength

30
*When taken as directed. See Drug Facts Panel. TABLETS (3 x 10) Orally Disintegrating Tablets